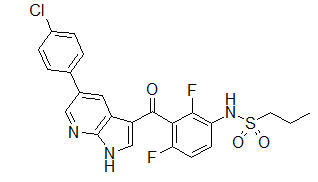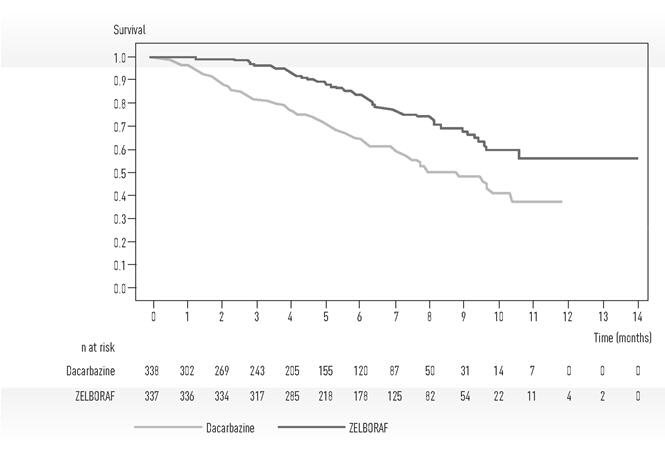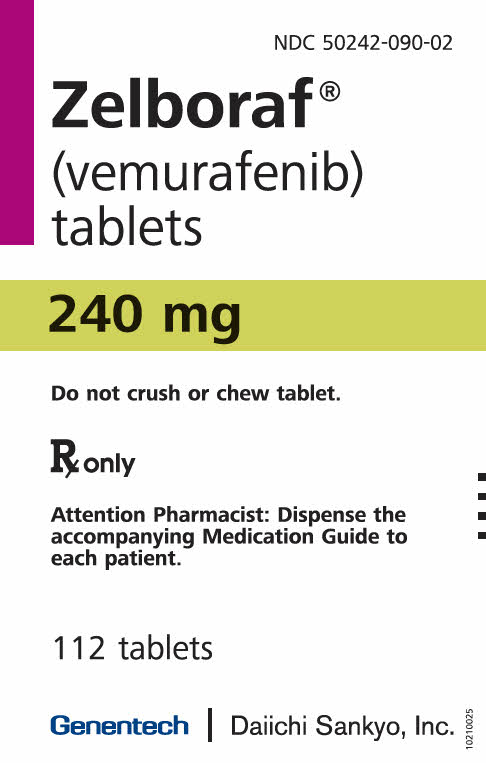 DRUG LABEL: ZELBORAF
NDC: 50242-090 | Form: TABLET, FILM COATED
Manufacturer: Genentech, Inc.
Category: prescription | Type: HUMAN PRESCRIPTION DRUG LABEL
Date: 20251201

ACTIVE INGREDIENTS: VEMURAFENIB 240 mg/1 1
INACTIVE INGREDIENTS: HYPROMELLOSE ACETATE SUCCINATE 16070722 (3 MPA.S); CROSCARMELLOSE SODIUM; HYDROXYPROPYL CELLULOSE (90000 WAMW); POLYVINYL ALCOHOL, UNSPECIFIED; TITANIUM DIOXIDE; POLYETHYLENE GLYCOL 3350; TALC; FERRIC OXIDE RED

HIGHLIGHTS OF PRESCRIBING INFORMATION

These highlights do not include all the information needed to use ZELBORAF safely and effectively. See full prescribing information for ZELBORAF.
ZELBORAF® (vemurafenib) tablet for oral use
Initial U.S. Approval: 2011

1 INDICATIONS AND USAGE

- ZELBORAF® is a kinase inhibitor indicated for the treatment of patients with unresectable or metastatic melanoma with BRAF V600E mutation as detected by an FDA-approved test. (1.1, 2.1)
- ZELBORAF® is indicated for the treatment of patients with Erdheim- Chester Disease with BRAF V600 mutation. (1.2, 2.1)

Limitation of Use: ZELBORAF is not indicated for treatment of patients with wild-type BRAF melanoma (2.1, 5.2)

2 DOSAGE AND ADMINISTRATION

- Confirm the presence of BRAF V600E mutation in tumor specimens prior to initiation of treatment with ZELBORAF. (2.1)
- Recommended dose: 960 mg orally twice daily taken approximately 12 hours apart with or without a meal. (2.2)

3 DOSAGE FORMS AND STRENGTHS

Tablet: 240 mg (3)

4 CONTRAINDICATIONS

None

5 WARNINGS AND PRECAUTIONS

- New Primary Cutaneous Malignancies: Perform dermatologic evaluations prior to initiation of therapy, every 2 months while on therapy, and for up to 6 months following discontinuation of ZELBORAF. Manage with excision and continue treatment without dose adjustment. (5.1)
- New Non-Cutaneous Squamous Cell Carcinoma: Evaluate for symptoms or clinical signs of new non-cutaneous SCC before initiation of treatment and periodically during treatment. (5.1)
- Other Malignancies: Monitor patients receiving ZELBORAF closely for signs or symptoms of other malignancies (5.1).
- Tumor Promotion in BRAF Wild-Type Melanoma: Increased cell proliferation can occur with BRAF inhibitors (5.2).
- Serious Hypersensitivity Reactions including anaphylaxis and Drug Reaction with Eosinophilia and Systemic Symptoms (DRESS Syndrome): Discontinue ZELBORAF for severe hypersensitivity reactions. (5.3)
- Severe Dermatologic Reactions, including Stevens-Johnson Syndrome and Toxic Epidermal Necrolysis: Discontinue ZELBORAF for severe dermatologic reactions. (5.4)
- QT Prolongation: Monitor ECG and electrolytes before and during treatment. Withhold ZELBORAF for QTc of 500 ms or greater. Correct electrolyte abnormalities and control for cardiac risk factors for QT prolongation. (5.5)
- Hepatotoxicity: Measure liver enzymes and bilirubin before initiating ZELBORAF and monitor monthly during treatment. (5.6)
- Photosensitivity: Advise patients to avoid sun exposure. (5.7)
- Serious Ophthalmologic Reactions: Monitor for signs and symptoms of uveitis. (5.8)
- Embryo-Fetal Toxicity: Can cause fetal harm. Advise females of the potential risk to the fetus and to use effective contraception. (5.9, 8.1, 8.3)
- Radiation Sensitization and Radiation Recall: Severe cases have been reported. (5.10).
- Renal Failure: Measure serum creatinine before initiating ZELBORAF and monitor periodically during treatment (5.11).
- Dupuytren's Contracture and plantar fascial fibromatosis: Events should be managed with dose reduction, treatment interruption, or treatment discontinuation. (5.12).

6 ADVERSE REACTIONS

Melanoma: Most common adverse reactions (≥ 30%) are arthralgia, rash, alopecia, fatigue, photosensitivity reaction, nausea, pruritus, and skin papilloma. (6.1)

Erdheim-Chester Disease: Most common adverse reactions (>50%) are arthralgia, rash maculo-papular, alopecia, fatigue, electrocardiogram QT interval prolonged, and skin papilloma. (6.1)

To report SUSPECTED ADVERSE REACTIONS, contact Genentech at 1-888-835-2555 or FDA at 1-800-FDA-1088 or www.fda.gov/medwatch.

7 DRUG INTERACTIONS

- Avoid concomitant administration of ZELBORAF with strong CYP3A4 inhibitors or inducers. (7.1)
- CYP1A2 Substrates: ZELBORAF can increase concentrations of CYP1A2 substrates. Avoid concomitant use of ZELBORAF with CYP1A2 substrates with a narrow therapeutic window. If coadministration cannot be avoided, monitor closely for toxicities and consider dose reduction of CYP1A2 substrates. (7.2).

8 USE IN SPECIFIC POPULATIONS

- Lactation: Do not breastfeed while taking ZELBORAF. (8.2)

FULL PRESCRIBING INFORMATION

1 INDICATIONS AND USAGE

1.1 Unresectable or Metastatic Melanoma

ZELBORAF® is indicated for the treatment of patients with unresectable or metastatic melanoma with BRAF V600E mutation as detected by an FDA-approved test.

Limitation of Use: ZELBORAF is not indicated for treatment of patients with wild-type BRAF melanoma [see Warnings and Precautions (5.2)].

1.2 Erdheim-Chester Disease

ZELBORAF® is indicated for the treatment of patients with Erdheim-Chester Disease (ECD) with BRAF V600 mutation.

2 DOSAGE AND ADMINISTRATION

2.1 Patient Selection for Treatment of Melanoma

Confirm the presence of BRAF V600E mutation in melanoma tumor specimens prior to initiation of treatment with ZELBORAF [see Warnings and Precautions (5.2)]. Information on FDA-approved tests for the detection of BRAF V600 mutations in melanoma is available at http://www.fda.gov/CompanionDiagnostics.

2.2 Recommended Dose

The recommended dose of ZELBORAF is 960 mg (four 240 mg tablets) orally every 12 hours with or without a meal. A missed dose can be taken up to 4 hours prior to the next dose.

Treat patients with ZELBORAF until disease progression or unacceptable toxicity occurs.

Do not take an additional dose if vomiting occurs after ZELBORAF administration, but continue with the next scheduled dose.

Do not crush or chew the tablets.

2.3 Dose Modifications

For New Primary Cutaneous Malignancies: No dose modifications are recommended.

For Other Adverse Reactions:

Permanently discontinue ZELBORAF for any of the following:

- Grade 4 adverse reaction, first appearance (if clinically appropriate) or second appearance
- QTc prolongation > 500 ms and increased by > 60 ms from pre-treatment values [see Warnings and Precautions (5.5)]

Withhold ZELBORAF for NCI-CTCAE (v4.0) intolerable Grade 2 or greater adverse reactions.

Upon recovery to Grade 0–1, restart ZELBORAF at a reduced dose as follows:

- 720 mg twice daily for first appearance of intolerable Grade 2 or Grade 3 adverse reactions
- 480 mg twice daily for second appearance of Grade 2 (if intolerable) or Grade 3 adverse reactions or for first appearance of Grade 4 adverse reaction (if clinically appropriate)

Do not dose reduce to below 480 mg twice daily.

2.4 Dose Modification for Strong CYP3A4 Inducers

Avoid concomitant use of strong CYP3A4 inducers during treatment with ZELBORAF [see Drug Interactions (7.1) and Clinical Pharmacology (12.3)]. If concomitant use of a strong CYP3A4 inducer is unavoidable, increase the dose of ZELBORAF by 240 mg (one tablet) as tolerated. After discontinuation of a strong CYP3A4 inducer for two weeks, resume the ZELBORAF dose that was taken prior to initiating the strong CYP3A4 inducer.

3 DOSAGE FORMS AND STRENGTHS

Tablet: 240 mg.

4 CONTRAINDICATIONS

None.

5 WARNINGS AND PRECAUTIONS

5.1 New Primary Malignancies

Cutaneous Malignancies

Cutaneous squamous cell carcinoma, keratoacanthoma, and melanoma occurred at a higher incidence in patients receiving ZELBORAF compared to those in the control arm in Trial 1. The incidence of cutaneous squamous cell carcinomas (cuSCC) and keratoacanthomas in the ZELBORAF arm was 24% compared to < 1% in the dacarbazine arm [see Adverse Reactions (6.1)]. The median time to the first appearance of cuSCC was 7 to 8 weeks; approximately 33% of patients who developed a cuSCC while receiving ZELBORAF experienced at least one additional occurrence with median time between occurrences of 6 weeks. Potential risk factors associated with cuSCC observed in clinical studies using ZELBORAF included age (≥ 65 years), prior skin cancer, and chronic sun exposure.

In Trial 4, in patients with ECD, the incidence of cuSCC and/or keratoacanthomas was 40.9% (9/22). The median time to first appearance of cuSCC amongst patients with at least one occurrence was 12.1 weeks.

In Trial 1, in patients with unresectable or metastatic melanoma, new primary malignant melanoma occurred in 2.1% (7/336) of patients receiving ZELBORAF compared to none of the patients receiving dacarbazine.

Perform dermatologic evaluations prior to initiation of therapy and every 2 months while on therapy. Manage suspicious skin lesions with excision and dermatopathologic evaluation. Consider dermatologic monitoring for 6 months following discontinuation of ZELBORAF.

Non-Cutaneous Squamous Cell Carcinoma

Non-cutaneous squamous cell carcinomas (non-cuSCC) of the head and neck can occur in patients receiving ZELBORAF [see Adverse Reactions (6.1)]. Monitor patients receiving ZELBORAF closely for signs or symptoms of new non-cuSCC.

Other Malignancies

Based on mechanism of action, ZELBORAF may promote malignancies associated with activation of RAS through mutation or other mechanisms [see Warnings and Precautions (5.2)]. Monitor patients receiving ZELBORAF closely for signs or symptoms of other malignancies.

Cases of myeloid neoplasms amongst patients with ECD have been observed, including in patients who have received ZELBORAF. Monitoring complete blood count in ECD patients with co-existing myeloid malignancies is recommended.

5.2 Tumor Promotion in BRAF Wild-Type Melanoma

In vitro experiments have demonstrated paradoxical activation of MAP-kinase signaling and increased cell proliferation in BRAF wild-type cells that are exposed to BRAF inhibitors. Confirm evidence of BRAF V600E mutation in tumor specimens prior to initiation of ZELBORAF [see Indications and Usage (1) and Dosage and Administration (2.1)].

5.3 Hypersensitivity Reactions

Anaphylaxis and other serious hypersensitivity reactions can occur during treatment and upon re-initiation of treatment with ZELBORAF. Severe hypersensitivity reactions included generalized rash and erythema, hypotension, and drug reaction with eosinophilia and systemic symptoms (DRESS syndrome). Permanently discontinue ZELBORAF in patients who experience a severe hypersensitivity reaction [see Adverse Reactions (6.2)].

5.4 Dermatologic Reactions

Severe dermatologic reactions, including Stevens-Johnson syndrome and toxic epidermal necrolysis, can occur in patients receiving ZELBORAF. Permanently discontinue ZELBORAF in patients who experience a severe dermatologic reaction [see Adverse Reactions (6.1)].

5.5 QT Prolongation

Concentration-dependent QT prolongation occurred in an uncontrolled, open-label QT sub-study in previously treated patients with BRAF V600E mutation-positive metastatic melanoma [see Clinical Pharmacology (12.2)]. QT prolongation may lead to an increased risk of ventricular arrhythmias, including Torsade de Pointes.

Do not start treatment in patients with uncorrectable electrolyte abnormalities, QTc > 500 ms, or long QT syndrome, or in patients who are taking medicinal products known to prolong the QT interval. Prior to and following treatment initiation or after dose modification of ZELBORAF for QTc prolongation, evaluate ECG and electrolytes (including potassium, magnesium, and calcium) after 15 days, monthly during the first 3 months, and then every 3 months thereafter or more often as clinically indicated.

Withhold ZELBORAF in patients who develop QTc > 500 ms (Grade 3). Upon recovery to QTc ≤ 500 ms (Grade ≤ 2), restart at a reduced dose. Permanently discontinue ZELBORAF treatment if the QTc interval remains > 500 ms and increased > 60 ms from pre-treatment values after controlling cardiac risk factors for QT prolongation (e.g., electrolyte abnormalities, congestive heart failure, and bradyarrhythmias) [see Dosage and Administration (2.3)].

5.6 Hepatotoxicity

Liver injury leading to functional hepatic impairment, including coagulopathy or other organ dysfunction, can occur with ZELBORAF [see Adverse Reactions (6.1)]. Monitor transaminases, alkaline phosphatase, and bilirubin before initiation of treatment and monthly during treatment, or as clinically indicated. Manage laboratory abnormalities with dose reduction, treatment interruption, or treatment discontinuation [see Dosage and Administration (2.3)].

Concurrent Administration with Ipilimumab

The safety and effectiveness of ZELBORAF in combination with ipilimumab have not been established [see Indications and Usage (1)]. In a dose-finding trial, Grade 3 increases in transaminases and bilirubin occurred in a majority of patients who received concurrent ipilimumab (3 mg/kg) and vemurafenib (960 mg BID or 720 mg BID) [see Drug Interactions (7.3)].

5.7 Photosensitivity

Mild to severe photosensitivity can occur in patients treated with ZELBORAF [see Adverse Reactions (6.1)]. Advise patients to avoid sun exposure, wear protective clothing and use a broad spectrum UVA/UVB sunscreen and lip balm (SPF ≥ 30) when outdoors.

Institute dose modifications for intolerable Grade 2 or greater photosensitivity [see Dosage and Administration (2.2)].

5.8 Ophthalmologic Reactions

Uveitis, blurry vision, and photophobia can occur in patients treated with ZELBORAF. In Trial 1, uveitis, including iritis, occurred in 2.1% (7/336) of patients receiving ZELBORAF compared to no patients in the dacarbazine arm. Treatment with steroid and mydriatic ophthalmic drops may be required to manage uveitis. Monitor patients for signs and symptoms of uveitis.

5.9 Embryo-Fetal Toxicity

Based on its mechanism of action, ZELBORAF can cause fetal harm when administered to a pregnant woman. Advise pregnant women of the potential risk to a fetus. Advise females of reproductive potential to use effective contraception during treatment with ZELBORAF and for 2 weeks after the final dose [see Use in Specific Populations (8.1, 8.3) and Clinical Pharmacology (12.1)].

5.10 Radiation Sensitization and Radiation Recall

Radiation sensitization and recall, in some cases severe, involving cutaneous and visceral organs have been reported in patients treated with radiation prior to, during, or subsequent to vemurafenib treatment. Fatal cases have been reported in patients with visceral organ involvement. [see Adverse Reactions (6.2)].

Monitor patients closely when vemurafenib is administered concomitantly or sequentially with radiation treatment.

5.11 Renal Failure

Renal failure, including acute interstitial nephritis and acute tubular necrosis, can occur with ZELBORAF. In Trial 1, in patients with metastatic melanoma, 26% of ZELBORAF-treated patients and 5% of dacarbazine-treated patients experienced Grade 1-2 creatinine elevations [greater than 1 and up to 3 times upper limit of normal (ULN)]; 1.2% of ZELBORAF-treated patients and 1.1% of dacarbazine-treated patients experienced Grade 3-4 creatinine elevations (greater than 3 times ULN).

In Trial 4, in patients with ECD, 86% (19/22) of patients experienced Grade 1/2 creatinine elevations and 9.1% (2/22) of patients experienced Grade 3 creatinine elevations.

Measure serum creatinine before initiation of ZELBORAF and periodically during treatment.

5.12 Dupuytren's Contracture and Plantar Fascial Fibromatosis

Dupuytren's contracture and plantar fascial fibromatosis have been reported with ZELBORAF. The majority of cases were mild to moderate, but severe, disabling cases of Dupuytren's contracture have also been reported [see Dosage and Administration (2.3), Adverse Reactions (6.1, 6.2)].

6 ADVERSE REACTIONS

The following adverse reactions are discussed in greater detail in other sections of the label:

- New Primary Malignancies [see Warnings and Precautions (5.1)]
- Hypersensitivity Reactions [see Warnings and Precautions (5.3)]
- Dermatologic Reactions [see Warnings and Precautions (5.4)]
- QT Prolongation [see Warnings and Precautions (5.5)]
- Hepatotoxicity [see Warnings and Precautions (5.6)]
- Photosensitivity [see Warnings and Precautions (5.7)]
- Ophthalmologic Reactions [see Warnings and Precautions (5.8)]
- Radiation Sensitization and Radiation Recall [see Warnings and Precautions (5.10)]
- Renal Failure [see Warnings and Precautions (5.11)]
- Dupuytren's Contracture and Plantar Fascial Fibromatosis [see Warnings and Precautions (5.12)]

6.1 Clinical Trials Experience

Because clinical studies are conducted under widely varying conditions, adverse reaction rates observed in the clinical studies of a drug cannot be directly compared to rates in the clinical studies of another drug and may not predict the rates observed in a broader patient population in clinical practice.

Unresectable or Metastatic Melanoma with BRAF V600E Mutation This section describes adverse drug reactions (ADRs) identified from analyses of Trial 1 and Trial 2 [see Clinical Studies (14)]. Trial 1 randomized (1:1) 675 treatment-naive patients with unresectable or metastatic melanoma to receive ZELBORAF 960 mg orally twice daily or dacarbazine 1000 mg/m^2 intravenously every 3 weeks. In Trial 2, 132 patients with metastatic melanoma and failure of at least one prior systemic therapy received treatment with ZELBORAF 960 mg orally twice daily.

Table 1 presents adverse reactions reported in at least 10% of unresectable or metastatic melanoma patients treated with ZELBORAF. The most common adverse reactions of any grade (≥ 30% in either study) in ZELBORAF-treated patients were arthralgia, rash, alopecia, fatigue, photosensitivity reaction, nausea, pruritus, and skin papilloma. The most common (≥ 5%) Grade 3 adverse reactions were cuSCC and rash. The incidence of Grade 4 adverse reactions was ≤ 4% in both studies.

The incidence of adverse events resulting in permanent discontinuation of study medication in Trial 1 was 7% for the ZELBORAF arm and 4% for the dacarbazine arm. In Trial 2, the incidence of adverse events resulting in permanent discontinuation of study medication was 3% in ZELBORAF-treated patients. The median duration of study treatment was 4.2 months for ZELBORAF and 0.8 months for dacarbazine in Trial 1, and 5.7 months for ZELBORAF in Trial 2.

Table 1 Adverse Reactions Reported in ≥ 10% of Unresectable or Metastatic Melanoma Patients Treated with ZELBORAF [Adverse drug reactions, reported using MedDRA and graded using NCI-CTC-AE v 4.0 (NCI common toxicity criteria) for assessment of toxicity.]
ADRs | Trial 1: Treatment-Naïve Patients |  |  |  | Trial 2: Patients with Failure of at Least One Prior Systemic Therapy
ADRs | ZELBORAF n=336 |  | Dacarbazine n=287 |  | ZELBORAF n=132
ADRs | All Grades (%) | Grade 3 [Grade 4 adverse reactions limited to gamma-glutamyltransferase increased (< 1% in Trial 1 and 4% in Trial 2).] (%) | All Grades (%) | Grade 3 (%) | All Grades (%) | Grade 3 (%)
Skin and subcutaneous tissue disorders
Rash | 37 | 8 | 2 | 0 | 52 | 7
Photosensitivity reaction | 33 | 3 | 4 | 0 | 49 | 3
Alopecia | 45 | < 1 | 2 | 0 | 36 | 0
Pruritus | 23 | 1 | 1 | 0 | 30 | 2
Hyperkeratosis | 24 | 1 | < 1 | 0 | 28 | 0
Rash maculo-papular | 9 | 2 | < 1 | 0 | 21 | 6
Actinic keratosis | 8 | 0 | 3 | 0 | 17 | 0
Dry skin | 19 | 0 | 1 | 0 | 16 | 0
Rash papular | 5 | < 1 | 0 | 0 | 13 | 0
Erythema | 14 | 0 | 2 | 0 | 8 | 0
Musculoskeletal and connective tissue disorders
Arthralgia | 53 | 4 | 3 | < 1 | 67 | 8
Myalgia | 13 | < 1 | 1 | 0 | 24 | < 1
Pain in extremity | 18 | < 1 | 6 | 2 | 9 | 0
Musculoskeletal pain | 8 | 0 | 4 | < 1 | 11 | 0
Back pain | 8 | < 1 | 5 | < 1 | 11 | < 1
General disorders and administration site conditions
Fatigue | 38 | 2 | 33 | 2 | 54 | 4
Edema peripheral | 17 | < 1 | 5 | 0 | 23 | 0
Pyrexia | 19 | < 1 | 9 | < 1 | 17 | 2
Asthenia | 11 | < 1 | 9 | < 1 | 2 | 0
Gastrointestinal disorders
Nausea | 35 | 2 | 43 | 2 | 37 | 2
Diarrhea | 28 | < 1 | 13 | < 1 | 29 | < 1
Vomiting | 18 | 1 | 26 | 1 | 26 | 2
Constipation | 12 | < 1 | 24 | 0 | 16 | 0
Nervous system disorders
Headache | 23 | < 1 | 10 | 0 | 27 | 0
Dysgeusia | 14 | 0 | 3 | 0 | 11 | 0
Neoplasms benign, malignant and unspecified (includes cysts and polyps)
Skin papilloma | 21 | < 1 | 0 | 0 | 30 | 0
Cutaneous SCC [Includes both squamous cell carcinoma of the skin and keratoacanthoma.] [Cases of cutaneous squamous cell carcinoma were required to be reported as Grade 3 per protocol.] | 24 | 22 | < 1 | < 1 | 24 | 24
Seborrheic keratosis | 10 | < 1 | 1 | 0 | 14 | 0
Investigations
Gamma-glutamyltransferase increased | 5 | 3 | 1 | 0 | 15 | 6
Metabolism and nutrition disorders
Decreased appetite | 18 | 0 | 8 | < 1 | 21 | 0
Respiratory, thoracic and mediastinal disorders
Cough | 8 | 0 | 7 | 0 | 12 | 0
Injury, poisoning and procedural complications
Sunburn | 10 | 0 | 0 | 0 | 14 | 0

Clinically relevant adverse reactions reported in < 10% of unresectable or metastatic melanoma patients treated with ZELBORAF in the Phase 2 and Phase 3 studies include:

Skin and subcutaneous tissue disorders: palmar-plantar erythrodysesthesia syndrome, keratosis pilaris, panniculitis, erythema nodosum, Stevens-Johnson syndrome, toxic epidermal necrolysis

Musculoskeletal and connective tissue disorders: arthritis, Dupuytren's contracture

Nervous system disorders: neuropathy peripheral, VIIth nerve paralysis

Neoplasms benign, malignant and unspecified (includes cysts and polyps): basal cell carcinoma, oropharyngeal squamous cell carcinoma

Infections and infestations: folliculitis

Eye disorders: retinal vein occlusion

Vascular disorders: vasculitis

Cardiac disorders: atrial fibrillation

Table 2 shows the incidence of worsening liver laboratory abnormalities in Trial 1 summarized as the proportion of patients who experienced a shift from baseline to Grade 3 or 4.

Table 2 Change from Baseline to Grade 3/4 Liver Laboratory Abnormalities in Trial 1 [For ALT, alkaline phosphatase, and bilirubin, there were no patients with a change to Grade 4 in either treatment arm.]
Parameter | Change From Baseline to Grade 3/4
Parameter | ZELBORAF (%) | Dacarbazine (%)
GGT | 11.5 | 8.6
AST | 0.9 | 0.4
ALT | 2.8 | 1.9
Alkaline phosphatase | 2.9 | 0.4
Bilirubin | 1.9 | 0

Erdheim-Chester Disease (ECD)

This section describes adverse reactions identified from analyses of Trial 4 [see Clinical Studies (14)]. In Trial 4, 22 patients with BRAF V600 mutation-positive ECD received ZELBORAF 960 mg twice daily.

The median treatment duration for ECD patients in this study was 14.2 months. Table 3 presents adverse reactions reported in at least 20% of BRAF V600 mutation-positive ECD patients treated with ZELBORAF.

In Trial 4, the most commonly reported adverse reactions (> 50%) in patients with BRAF V600 mutation- positive ECD treated with ZELBORAF were arthralgia, rash maculo-papular, alopecia, fatigue, electrocardiogram QT interval prolonged, and skin papilloma. The most common (≥ 10%) Grade ▯ 3 adverse reactions were squamous cell carcinoma of the skin, hypertension, rash maculo-papular, and arthralgia.

The incidence of adverse reactions resulting in permanent discontinuation of study medication was 32%.

Table 3 Adverse Reactions Reported in ≥ 20% of ECD Patients Treated with ZELBORAF [Adverse drug reactions, graded using NCI-CTCAE v 4.0 (NCI common toxicity criteria) for assessment of toxicity.]
Trial 4: Patients with ECD
 | n=22
Body System Adverse Reactions | All Grades (%) | Grade 3-4 (%)
Skin and subcutaneous tissue disorders
Rash maculo-papular | 59 | 18
Alopecia | 55 | -
Hyperkeratosis | 50 | 5
Dry skin | 45 | -
Photosensitivity reaction | 41 | -
Palmar-plantar erythrodysaesthesia syndrome | 41 | -
Pruritus | 36 | -
Actinic keratosis | 32 | 5
Keratosis pilaris | 32 | -
Rash papular | 23 | -
Musculoskeletal and connective tissue disorders
Arthralgia | 82 | 14
General disorders and administration site conditions
Fatigue | 55 | 5
Gastrointestinal disorders
Diarrhea | 50 | -
Nausea | 32 | -
Vomiting | 23 | -
Nervous system disorders
Peripheral sensory neuropathy | 36 | -
Neoplasms benign, malignant and unspecified (incl. cysts and polyps)
Skin papilloma | 55 | -
Seborrhoeic keratosis | 41 | -
SCC of skin [Cases of cutaneous squamous cell carcinoma were required to be reported as Grade 3 per protocol.] | 36 | 36
Melanocytic nevus | 23 | _
Cardiac disorders
Electrocardiogram QT interval prolonged | 55 | 5
Respiratory, thoracic and mediastinal disorders
Cough | 36 | -
Vascular disorders
Hypertension | 36 | 23
Injury, poisoning and procedural complications
Sunburn | 23 | -

Clinically relevant adverse reactions reported in < 20% of ECD patients treated with ZELBORAF in Trial 4 include:

Neoplasms benign, malignant and unspecified (includes cysts and polyps): keratoacanthoma

Musculoskeletal and connective tissue disorders: Dupuytren's contracture

Table 4 shows the incidence of worsening liver laboratory abnormalities in Trial 4 summarized as the proportion of ECD patients who experienced a shift from baseline to Grade 3 or 4.

Table 4 Change from Baseline to Grade 3 Liver Laboratory Abnormalities in Trial 4
 | Change From Baseline to Grade 3
Parameter | Vemurafenib (%)
AST | 0
ALT | 9.1
Alkaline phosphatase | 4.5
Bilirubin | 0

6.2 Postmarketing Experience

The following adverse reactions have been identified during post approval use of ZELBORAF. Because these reactions are reported voluntarily from a population of uncertain size, it is not always possible to reliably estimate their frequency or establish a causal relationship to drug exposure.

Neoplasms benign, malignant and unspecified (incl. cysts and polyps): Progression of pre-existing chronic myelomonocytic leukemia with NRAS mutation [see Warnings and Precautions (5.1)].

Skin and subcutaneous tissue disorders: Drug reaction with eosinophilia and systemic symptoms (DRESS syndrome) [see Warnings and Precautions (5.3)].

Blood and lymphatic systems disorder: Neutropenia

Injury, poisoning and procedural complications: Radiation sensitization and recall [see Warnings and Precautions (5.10)].

Gastrointestinal disorders: Pancreatitis

Renal and urinary disorders: Acute interstitial nephritis, acute tubular necrosis [see Warnings and Precautions (5.11)].

Musculoskeletal and connective tissue disorders: Dupuytren's contracture and plantar fascial fibromatosis [see Warnings and Precautions (5.12)].

7 DRUG INTERACTIONS

7.1 Effect of Strong CYP3A4 Inhibitors or Inducers on Vemurafenib

Strong CYP3A4 Inhibitors

Coadministration of a strong CYP3A4 inhibitor increased vemurafenib plasma concentrations and may lead to increased toxicity. Avoid coadministration of ZELBORAF with strong CYP3A4 inhibitors. If coadministration of a strong CYP3A4 inhibitor is unavoidable, consider dose reduction of ZELBORAF, if clinically indicated. [see Dosage and Administration (2.3), Clinical Pharmacology (12.3)].

Strong CYP3A4 Inducers

Coadministration of ZELBORAF with rifampin, a strong CYP3A4 inducer, decreased vemurafenib plasma concentrations and may result in decreased efficacy. Avoid coadministration of ZELBORAF with strong CYP3A4 inducers (e.g., phenytoin, carbamazepine, rifampin), and replace these drugs with alternative drugs when possible. If coadministration of a strong CYP3A4 inducer is unavoidable, increase the dose of ZELBORAF by 240 mg (one tablet) as tolerated [see Dosage and Administration (2.4), Clinical Pharmacology (12.3)].

7.2 Effect of Vemurafenib on CYP1A2 Substrates

Coadministration of ZELBORAF with tizanidine, a sensitive CYP1A2 substrate, increased tizanidine systemic exposure by 4.7-fold. Avoid concomitant use of ZELBORAF with drugs having a narrow therapeutic window that are predominantly metabolized by CYP1A2 [see Clinical Pharmacology (12.3)]. If coadministration cannot be avoided, monitor closely for toxicities and consider a dose reduction of concomitant CYP1A2 substrates.

7.3 Concurrent Ipilimumab

Increases in transaminases and bilirubin occurred in a majority of patients who received concurrent ipilimumab and ZELBORAF [see Warnings and Precautions Section 5.6].

7.4 Effect of Vemurafenib on P-gp Substrates

Coadministration of ZELBORAF with digoxin, a sensitive P-glycoprotein (P-gp) substrate, increased digoxin systemic exposure by 1.8-fold. Avoid concurrent use of P-gp substrates known to have narrow therapeutic indices. If use of these medications is unavoidable, consider dose reduction of P-gp substrates with narrow therapeutic indices.

8 USE IN SPECIFIC POPULATIONS

8.1 Pregnancy

Risk Summary

Based on its mechanism of action, ZELBORAF can cause fetal harm when administered to a pregnant woman [see Clinical Pharmacology (12.1)]. There are no available data on the use of ZELBORAF in pregnant women to determine the drug-associated risk; however, placental transfer of vemurafenib to a fetus has been reported. Exposure to vemurafenib could not be achieved in animals at levels sufficient to fully address its potential toxicity in pregnant women. Advise pregnant women of the potential harm to a fetus.

The estimated background risks of major birth defects and miscarriage for the indicated population(s) are unknown. In the U.S. general population, the estimated background risk of major birth defects and miscarriage in clinically recognized pregnancies is 2-4% and 15-20%, respectively.

Data

Animal Data

Vemurafenib showed no evidence of developmental toxicity in rat fetuses at doses up to 250 mg/kg/day (approximately 1.3 times the clinical exposure at 960 mg twice daily based on AUC) or rabbit fetuses at doses up to 450 mg/kg/day (approximately 0.6 times the clinical exposure at 960 mg twice daily based on AUC). Fetal drug levels were 3–5% of maternal levels, indicating that vemurafenib has the potential to be transmitted from the mother to the developing fetus.

8.2 Lactation

There is no information available regarding the presence of vemurafenib in human milk, effects on the breastfed infant, or effects on milk production. Because of the potential for serious adverse reactions in a breastfed infant, including malignancy, severe dermatologic reactions, QT prolongation, hepatotoxicity, photosensitivity, and ophthalmologic toxicity, [see Warnings and Precautions (5)], advise women not to breastfeed during treatment with ZELBORAF and for 2 weeks after the final dose.

8.3 Females and Males of Reproductive Potential

Contraception

Based on its mechanism of action, ZELBORAF can cause fetal harm when administered to a pregnant woman [see Use in Specific Populations (8.1)]. Advise females of reproductive potential to use effective contraception during treatment with ZELBORAF and for 2 weeks after the final dose.

8.4 Pediatric Use

The safety and effectiveness of ZELBORAF in pediatric patients have not been established. Vemurafenib was studied in 6 adolescent patients 15 to 17 years of age with unresectable or metastatic melanoma with BRAF V600 mutation. A maximum tolerated dose was not reached with doses up to vemurafenib 960 mg twice daily. No new safety signals were observed. Vemurafenib steady-state exposure in these 6 adolescent patients was generally similar to that in adults.

8.5 Geriatric Use

Clinical studies of ZELBORAF did not include sufficient numbers of subjects aged 65 and over to determine whether they respond differently from younger subjects.

8.6 Hepatic Impairment

No formal clinical study has been conducted to evaluate the effect of hepatic impairment on the pharmacokinetics of vemurafenib. No dose adjustment is recommended for patients with mild and moderate hepatic impairment based on a population pharmacokinetic analysis [see Clinical Pharmacology (12.3)]. The appropriate dose of ZELBORAF has not been established in patients with severe hepatic impairment.

8.7 Renal Impairment

No formal clinical study has been conducted to evaluate the effect of renal impairment on the pharmacokinetics of vemurafenib. No dose adjustment is recommended for patients with mild and moderate renal impairment based on a population pharmacokinetic analysis [see Clinical Pharmacology (12.3)]. The appropriate dose of ZELBORAF has not been established in patients with severe renal impairment.

10 OVERDOSAGE

There is no information on overdosage of ZELBORAF.

11 DESCRIPTION

ZELBORAF (vemurafenib) is a kinase inhibitor available as 240 mg tablets for oral use. Vemurafenib has the chemical name propane-1-sulfonic acid {3-[5-(4-chlorophenyl)-1H-pyrrolo[2,3-b]pyridine-3-carbonyl]- 2,4-difluoro-phenyl}-amide. It has the molecular formula C23H18ClF2N3O3S and a molecular weight of 489.9. Vemurafenib has the following chemical structure:

Vemurafenib is a white to off-white crystalline solid. It is practically insoluble in aqueous media.

Tablets of ZELBORAF are for oral administration. Each tablet contains 240 mg of vemurafenib.

The inactive ingredients of ZELBORAF are: Tablet core: hypromellose acetate succinate, croscarmellose sodium, colloidal silicon dioxide, magnesium stearate, and hydroxypropyl cellulose. Coating: pinkish white: poly (vinyl alcohol), titanium dioxide, polyethylene glycol 3350, talc, and iron oxide red.

12 CLINICAL PHARMACOLOGY

12.1 Mechanism of Action

Vemurafenib is a low molecular weight, orally available inhibitor of some mutated forms of BRAF serine- threonine kinase, including BRAF V600E. Vemurafenib also inhibits other kinases in vitro such as CRAF, ARAF, wild-type BRAF, SRMS, ACK1, MAP4K5, and FGR at similar concentrations. Some mutations in the BRAF gene including V600E result in constitutively activated BRAF proteins, which can cause cell proliferation in the absence of growth factors that would normally be required for proliferation. Vemurafenib has anti-tumor effects in cellular and animal models of melanomas with mutated BRAF V600E.

12.2 Pharmacodynamics

Cardiac Electrophysiology

In a multi-center, open-label, single-arm study in 132 patients with BRAF V600E mutation-positive metastatic melanoma, patients administered vemurafenib 960 mg orally twice daily did not experience large changes in mean QTc interval (i.e., > 20 ms) from baseline. Vemurafenib is associated with concentration- dependent QTc interval prolongation. The largest mean change from baseline in the first month of treatment occurred at 2 hours post-dose on Day 15—an increase of 12.8 ms (upper boundary of the two-sided 90% confidence interval of 14.9 ms). In the first 6 months of treatment, the largest observed mean change from baseline occurred at a pre-dose time point—an increase of 15.1 ms (upper boundary of the two-sided 90% confidence interval of 17.7 ms).

12.3 Pharmacokinetics

The pharmacokinetics of vemurafenib were determined in patients with BRAF mutation-positive metastatic melanoma following 15 days of 960 mg twice daily with dosing approximately 12 hours apart. The population pharmacokinetic analysis pooled data from 458 patients. At steady-state, vemurafenib exhibits linear pharmacokinetics within the 240 mg to 960 mg dose range.

Absorption

The mean bioavailability of vemurafenib at steady state was 64% (56% CV). The median time to reach maximum plasma vemurafenib concentration (Tmax) was 3 hours following multiple doses.

The mean (± SD) Cmax and AUC0-12 were 62 ± 17 µg/mL and 601 ± 170 µg*h/mL, respectively. The median accumulation ratio estimate from the population pharmacokinetic analysis for the twice daily regimen is 7.4, with steady-state achieved at approximately 15 to 22 days.

In clinical trials, vemurafenib was administered without regard to food. A food effect study has demonstrated that a single dose of vemurafenib administered with a high-fat meal increased AUC by approximately 5-fold, increased Cmax by 2.5-fold, and delayed Tmax by approximately 4 hours as compared to the fasted state.

QTc prolongation may occur with increased exposures as vemurafenib is associated with concentration-dependent QTc interval prolongation [see Clinical Pharmacology (12.2)].

Distribution

Vemurafenib is highly bound (> 99%) to human albumin and alpha-1 acid glycoprotein plasma proteins. The population apparent volume of distribution is estimated to be 106 L (with 66% inter-patient variability).

Metabolism

Following oral administration of 960 mg of ^14C-vemurafenib, mean data showed that vemurafenib and its metabolites represented 95% and 5% of the components in plasma over 48 hours, respectively.

Elimination

Following oral administration of 960 mg of ^14C-vemurafenib, approximately 94% of the radioactive dose was recovered in feces and approximately 1% was recovered in the urine. The population apparent clearance is estimated to be 31 L/day (with 32% inter-patient variability). The median elimination half-life estimate for vemurafenib is 57 hours (the 5th and 95th percentile range is 30 to 120 hours).

Specific Populations

Hepatic Impairment: The pharmacokinetics of vemurafenib were examined in patients with metastatic melanoma enrolled in the clinical trials with normal hepatic function (n=158, total bilirubin ≤ ULN) and mild (n=58, total bilirubin 1.0–1.5 × ULN), moderate (n=27, total bilirubin 1.5–3 × ULN), or severe (n=3, total bilirubin > 3 × ULN) hepatic impairment. Patients received vemurafenib 960 mg orally twice daily. The apparent clearance of vemurafenib in patients with mild and moderate hepatic impairment was similar to that in patients with normal hepatic function. The appropriate dose for patients with severe hepatic impairment cannot be determined as clinical and pharmacokinetic data were available for only three patients [see Use in Specific Populations (8.6)].

Renal Impairment: The pharmacokinetics of vemurafenib were examined in patients with metastatic melanoma enrolled in the clinical trials with normal renal function (CLcr ≥ 90 mL/min) and mild (n=94, CLcr > 60 to 89 mL/min), moderate (n=11, CLcr 30 to 59 mL/min) or severe (n=1, CLcr < 29 mL/min) renal impairment. Patients received vemurafenib 960 mg orally twice daily. The apparent clearance of vemurafenib in patients with mild and moderate renal impairment was similar to that in patients with normal renal function. The appropriate dose for patients with severe renal impairment cannot be determined as clinical and pharmacokinetic data were available for only one patient [see Use in Specific Populations (8.7)].

Age, Body Weight, Sex, and Race: Based on the population pharmacokinetic analysis, age, body weight, and sex do not have a clinically important effect on the exposure of vemurafenib. There are insufficient data to evaluate potential differences in the pharmacokinetics of vemurafenib by race.

Drug Interaction Studies

Effect of Strong CYP3A4 Inhibitors: Coadministration of 960 mg ZELBORAF twice daily with once daily doses of 200 mg itraconazole, a strong CYP3A4 inhibitor, increased steady state vemurafenib AUC0-τ by 40% (90% CI: 21%, 61%) with a similar magnitude of increase in Cmax [see Drug Interactions (7.1)].

Effect of Strong CYP3A4 Inducers: Coadministration of 600 mg daily doses of rifampin (a strong CYP3A inducer) with a single 960 mg dose of ZELBORAF decreased vemurafenib AUC by 40% (90% CI: 24%, 53%) with no effect on Cmax, relative to a 960 mg dose of ZELBORAF administered alone [see Dosage and Administration (2.4), Drug Interactions (7.1)].

Effect of Vemurafenib on CYP Substrates: In vitro studies suggest that vemurafenib is an inhibitor of CYP1A2, 2A6, 2B6, 2C8, 2C9, 2C19, 2D6, and 3A4/5.

Coadministration of tizanidine 2 mg (a sensitive CYP1A2 substrate) on day 21 with vemurafenib which was administered 960 mg twice daily for 21 days increased tizanidine AUCinf by 4.7-fold (90% CI: 3.6, 6.3) and Cmax by 2.2-fold (90% CI: 1.7, 2.7) in 16 cancer patients [see Drug Interactions (7.2)]. In an in vivo phenotypic cocktail drug-drug interaction study in patients with cancer, a single dose of the CYP probe substrate cocktail (for CYP1A2, 2D6, 3A4, 2C19 and 2C9) was administered before and concomitantly with vemurafenib (following 15 days of dosing at 960 mg twice daily). Coadministration of vemurafenib increased the mean AUC of caffeine (CYP1A2 substrate) by 2.6-fold [see Drug Interactions (7.2)]. Coadministration of vemurafenib increased the mean AUC of dextromethorphan (CYP2D6 substrate) by 47% and the AUC of S-warfarin (CYP2C9 substrate) by 18%, while it decreased the mean AUC of midazolam (CYP3A4 substrate) by 39%. Coadministration of vemurafenib did not change the mean systemic exposure to omeprazole (CYP2C19 substrate).

Effect of Vemurafenib on Transporters: In vitro studies suggest that vemurafenib is both a substrate and an inhibitor of the efflux transporters P-glycoprotein (P-gp) and Breast Cancer Resistance Protein (BCRP).

Administration of vemurafenib 960 mg twice daily for 22 days increased digoxin AUC by 1.8-fold (90% CI:1.6, 2.0) and Cmax by 1.5-fold (90% CI:1.3, 1.7) in 26 cancer patients who were coadministered a single dose of digoxin 0.25 mg (sensitive P-gp substrate) [see Drug Interactions (7.4)].

13 NONCLINICAL TOXICOLOGY

13.1 Carcinogenesis, Mutagenesis, Impairment of Fertility

There have been no formal studies conducted assessing the carcinogenic potential of vemurafenib. ZELBORAF increased the development of cutaneous squamous cell carcinomas in patients in clinical trials.

Vemurafenib did not cause genetic damage when tested in in vitro assays (bacterial mutation [AMES Assay], human lymphocyte chromosome aberration) or in the in vivo rat bone marrow micronucleus test.

No specific studies with vemurafenib have been conducted in animals to evaluate the effect on fertility; nevertheless, no histopathological findings were noted in reproductive organs in males and females in repeat-dose toxicology studies in rats at doses up to 450 mg/kg/day (approximately 0.6 and 1.6 times the human exposure based on AUC in males and females, respectively) and dogs at doses up to 450 mg/kg/day (approximately 0.3 times the human clinical exposure based on AUC in both males and females, respectively).

13.2 Animal Toxicology and/or Pharmacology

Consistent with the increased incidence of cutaneous squamous cell carcinomas in patients treated with vemurafenib, the treatment of mice implanted with human cuSCC cells with vemurafenib caused a dose- dependent acceleration of the growth of the implanted tumors.

14 CLINICAL STUDIES

Treatment-Naïve Patients with BRAF V600E Mutation-Positive Unresectable or Metastatic Melanoma

Trial 1, an international, open-label, randomized controlled trial, equally allocated 675 patients with treatment-naive, BRAF V600E mutation-positive unresectable or metastatic melanoma, as detected by the cobas® 4800 BRAF V600 Mutation Test, to receive ZELBORAF 960 mg by mouth twice daily (n=337) or dacarbazine 1000 mg/m^2 intravenously on Day 1 every 3 weeks (n=338). Randomization stratification factors were disease stage, lactate dehydrogenase (LDH), ECOG performance status, and geographic region. Treatment continued until disease progression, unacceptable toxicity, and/or consent withdrawal. The major efficacy outcome measures of the trial were overall survival (OS) and investigator-assessed progression-free survival (PFS). Other outcome measures included confirmed investigator-assessed best overall response rate.

Baseline characteristics were balanced between treatment groups. Most patients were male (56%) and Caucasian (99%), the median age was 54 years (24% were ≥ 65 years), all patients had ECOG performance status of 0 or 1, and the majority of patients had metastatic disease (95%).

Trial 1 demonstrated statistically significant increases in overall survival and progression-free survival in the ZELBORAF arm compared to the dacarbazine control arm. Table 5 and Figure 1 summarize the efficacy results.

Table 5 Efficacy of ZELBORAF in Treatment-Naïve Patients with BRAF V600E Mutation-Positive Melanoma [As detected by the cobas® 4800 BRAF V600 Mutation Test]
 | ZELBORAF (n=337) | Dacarbazine (n=338) | p-value [Unstratified log-rank test]
Overall Survival
Number of Deaths [Total of 200 deaths (ZELBORAF median follow-up 6.2 months)] | 78 (23%) | 122 (36%)
Hazard Ratio (95% CI) [Hazard ratio estimated using Cox model; a hazard ratio of < 1 favors ZELBORAF] | 0.47 (0.35, 0.62) |  | < 0.0001
Updated Median Survival (months) (95 % CI) [Kaplan-Meier estimate] , [Updated based on 478 deaths (ZELBORAF median follow-up 13.4 months)] | 13.6 (12.0, 15.3) | 10.3 (9.1, 12.8) | -
Progression-Free Survival
Hazard Ratio (95% CI) | 0.26 (0.20, 0.33) |  | < 0.0001
Median PFS (months) (95% CI) | 5.3 (4.9, 6.6) | 1.6 (1.6, 1.7) | -

Figure 1 Kaplan-Meier Curves of Overall Survival – Treatment-Naïve Patients

The confirmed, investigator-assessed best overall response rate was 48.4% (95% CI: 41.6%, 55.2%) in the ZELBORAF arm compared to 5.5% (95% CI: 2.8%, 9.3%) in the dacarbazine arm. There were 2 complete responses (0.9%) and 104 partial responses (47.4%) in the ZELBORAF arm and all 12 responses were partial responses (5.5%) in the dacarbazine arm.

Patients with BRAF V600E Mutation-Positive Metastatic Melanoma Who Received Prior Systemic Therapy

In a single-arm, multicenter, multinational trial (Trial 2), 132 patients with BRAF V600E mutation-positive metastatic melanoma, as detected by the cobas® 4800 BRAF V600 Mutation Test, who had received at least one prior systemic therapy, received ZELBORAF 960 mg by mouth twice daily. The median age was 52 years with 19% of patients being older than 65 years. The majority of patients were male (61%) and Caucasian (99%). Forty-nine percent of patients received ≥ 2 prior therapies. The median duration of follow-up was 6.87 months (range, 0.6 to 11.3).

The confirmed best overall response rate as assessed by an independent review committee (IRC) was 52% (95% CI: 43%, 61%). There were 3 complete responses (2.3%) and 66 partial responses (50.0%). The median time to response was 1.4 months with 75% of responses occurring by month 1.6 of treatment. The median duration of response by IRC was 6.5 months (95% CI: 5.6, not reached).

Patients with BRAF V600E Mutation-Positive Melanoma with Brain Metastases

The activity of ZELBORAF for the treatment of BRAF V600E mutation-positive melanoma, metastatic to the brain was evaluated in an open-label, multicenter, single-arm, two cohort trial (Trial 3). All patients received ZELBORAF 960 mg orally twice daily until disease progression or unacceptable toxicity. Patients were required to have at least one measurable brain lesion of 0.5 cm or greater on contrast-enhanced MRI, a stable or decreasing corticosteroid dose and no prior treatment with a BRAF or MEK inhibitor. Patients in Cohort A had received no prior local therapy for brain metastases. Patients in Cohort B had received at least one prior local therapy for brain metastases (surgical resection, whole brain radiotherapy, or stereotactic radiotherapy) with CNS progression following this therapy. Patients were followed until death, disease progression, withdrawal, or up to 24 months. The primary efficacy outcome measure was the confirmed best overall response rate in the brain in Cohort A, as assessed by an independent radiology review committee using Response Evaluation Criteria in Solid Tumors (RECIST v1.1). Secondary efficacy outcome measures included duration of response in Cohort A, and confirmed best overall response rate and duration of response in Cohort B.

A total of 146 patients (Cohort A: n=90; Cohort B: n=56) were enrolled and received at least one dose of ZELBORAF. In Cohort A, the median age of patients was 56 years, 62% were male, 47% had a pre- treatment ECOG performance status (PS) of 0, 57% had an elevated LDH value at baseline, and 20% received one or more systemic regimens for the treatment of metastatic disease. In Cohort B, the median age of patients was 53 years, 61% were male, 38% had a pre-treatment ECOG PS of 0, 55% had an elevated LDH value at baseline, and 39% received one or more systemic regimens for the treatment of metastatic disease. All patients enrolled on Trial 3 whose race was identified were White. The efficacy results are summarized in Table 6.

Table 6 Efficacy Results in Patients with BRAF V600E Melanoma Brain Metastases
 | Cohort A (n=90) | Cohort B (n=56)
Confirmed Best Overall Response Rate in Brain, 95%CI [Two-sided 95% Clopper-Pearson Confidence Interval (CI)] | 18% (11%, 27%) | 18% (9%, 30%)
Complete response | 2% | 0
Partial response | 16% | 18%
Median of Duration of Response, months (95%CI [Kaplan-Meier estimate]) | 4.6 (2.9, 6.2) | 6.6 (2.8, 10.7)

Patients with Wild-Type BRAF Melanoma

ZELBORAF has not been studied in patients with wild-type BRAF melanoma [see Warnings and Precautions (5.2)].

Patients with Erdheim-Chester Disease (ECD)

An open-label, multicenter, single-arm, multiple cohort study of ZELBORAF (Trial 4) was conducted in patients ≥ 16 years of age with non-melanoma BRAF V600 mutation–positive diseases.

The trial included 22 patients with ECD. Fifteen patients (68.2%) had received prior systemic therapies. The median age was 58.5 years (range, 34 to 77 years). Fifty-five percent of patients were men.

All 22 patients received a starting dose of 960 mg orally twice daily with or without food. For 8 patients, the dose was reduced to 720 mg twice daily. For the remaining 14 patients, the dose was ultimately reduced to 480 mg. The median duration of treatment following a dose reduction to 720 mg was 77 days (range, 4 to 1325) and to 480 mg was 236 days (range, 21 to 924). The efficacy was maintained in these patients based on the overall response rate.

The efficacy of ZELBORAF in ECD was based on best overall response rate maintained on two occasions at least four weeks apart, as assessed by the investigator using RECIST v 1.1, and is presented in Table 7 below. The median duration of follow up was 26.6 months in ECD patients (range, 3.0 to 44.3 months). The median time to response was 11 months (95% CI: 3.7, 14.6). The median DOR was not estimable.

Table 7 Efficacy of ZELBORAF in patients with ECD (investigator assessed)
 | N=22
Overall Response
Responders (n [%]) | 12 (54.5%)
(95% CI) [95% Confidence Interval (CI) constructed using Clopper-Pearson method] | (32.2, 75.6)
Complete Response (CR) | 1 (4.5%)
Partial Response (PR) | 11 (50%)

16 HOW SUPPLIED/STORAGE AND HANDLING

ZELBORAF (vemurafenib) is supplied as 240 mg film-coated tablets with VEM debossed on one side. The following packaging configurations are available:

NDC 50242-090-01 single bottle of 120 count

NDC 50242-090-02 single bottle of 112 count

STORAGE AND HANDLING

Storage and Stability: Store at room temperature 20°C–25°C (68°F–77°F); excursions permitted between 15°C and 30°C (59°F and 86°F), See USP Controlled Room Temperature. Store in the original container with the lid tightly closed.

Disposal of unused/expired medicines: The release of pharmaceuticals in the environment should be minimized. Medicines should not be disposed of via wastewater and disposal through household waste should be avoided. Use established "collection systems," if available in your location.

17 PATIENT COUNSELING INFORMATION

Advise the patient to read the FDA-approved patient labeling (Medication Guide).

Healthcare providers should advise patients of the potential benefits and risks of ZELBORAF and instruct their patients to read the Medication Guide before starting ZELBORAF therapy. Inform patients of the following:

- Evidence of BRAF V600E mutation in the tumor specimen with an FDA approved test is necessary to identify patients with melanoma for whom treatment with ZELBORAF is indicated [see Dosage and Administration (2.1)].
- ZELBORAF increases the risk of developing new primary cutaneous malignancies. Advise patients of the importance of contacting their healthcare provider immediately for any changes in their skin [see Warnings and Precautions (5.1)].
- Anaphylaxis and other serious hypersensitivity reactions can occur during treatment and upon re- initiation of treatment with ZELBORAF. Advise patients to stop taking ZELBORAF and to seek immediate medical attention for symptoms of anaphylaxis or hypersensitivity [see Warnings and Precautions (5.3)].
- Severe dermatologic reactions can occur in patients receiving ZELBORAF. Advise patients to stop taking ZELBORAF and to contact their health-care provider for severe dermatologic reactions [see Warnings and Precautions (5.4)].
- ZELBORAF can prolong QT interval, which may result in ventricular arrhythmias. Advise patients of the importance of monitoring of their electrolytes and the electrical activity of their heart (via an ECG) during ZELBORAF treatment [see Warnings and Precautions (5.5)].
- Liver injury leading to functional hepatic impairment, including coagulopathy or other organ dysfunction, can occur with ZELBORAF. Advise patients of the importance of laboratory monitoring of their liver during ZELBORAF treatment and to contact their health-care provider for relevant symptoms [see Warnings and Precautions (5.6)].
- ZELBORAF can cause mild to severe photosensitivity. Advise patients to avoid sun exposure, wear protective clothing, and use a broad spectrum UVA/UVB sunscreen and lip balm (SPF ≥ 30) when outdoors to help protect against sunburn [see Warnings and Precautions (5.7)].
- Ophthalmologic reactions can occur in patients treated with ZELBORAF. Advise patients to contact their health-care provider immediately for ophthalmologic symptoms [see Warnings and Precautions (5.8)].

Embryo-fetal Toxicity

- Advise pregnant women and females of reproductive potential of the potential risk to a fetus [see Warnings and Precautions (5.9) and Use in Special Populations (8.1)].
- Advise females of reproductive potential to use effective contraception during treatment with ZELBORAF and for 2 weeks after the final dose [see Warnings and Precautions (5.9) and Use in Special Populations (8.1, 8.3)].
- Advise female patients to contact their health-care provider immediately with a known or suspected pregnancy [see Warnings and Precautions (5.9) and Use in Special Populations (8.1, 8.3)].

Lactation

- Advise a woman not to breastfeed during treatment with ZELBORAF and for 2 weeks after the final dose [see Use in Specific Populations (8.2)].
- Radiation sensitization and recall can occur in patients treated with radiation prior to, during, or subsequent to ZELBORAF treatment. Advise patients to inform their health care provider if they have had or are planning to receive radiation therapy [see Warnings and Precautions (5.10), Adverse Reactions (6.2)].
- Renal failure can occur in patients treated with ZELBORAF. Advise patients of the importance of monitoring serum creatinine prior to and during ZELBORAF treatment [see Warnings and Precautions (5.11), Adverse Reactions (6.2)].
- Advise patients to contact their health care provider for symptoms of Dupuytren's contracture or plantar fascial fibromatosis [see Warnings and Precautions (5.12)].

Distributed by:
Genentech USA, Inc.
A Member of the Roche Group
1 DNA Way
South San Francisco, CA 94080-4990

ZELBORAF is a registered trademark of Genentech, Inc.
Co-promoted by: Genentech USA, Inc. and Daiichi Sankyo, Inc.
©2020 Genentech, Inc.

MEDICATION GUIDE
ZELBORAF® (ZEL-bor-raf)
(vemurafenib)
tablet

What is the most important information I should know about ZELBORAF?

ZELBORAF can cause serious side effects, including:

Risk of new cancers. ZELBORAF may cause certain types of skin cancer called cutaneous squamous cell carcinoma (cuSCC) and keratoacanthoma. New melanoma lesions have occurred in people who take ZELBORAF. ZELBORAF may also cause another type of cancer called non-cutaneous squamous cell carcinoma (non-cuSCC). Talk with your healthcare provider about your risk for these cancers.

Check your skin and tell your healthcare provider right away about any skin changes including a:

- new wart
- skin sore or reddish bump that bleeds or does not heal
- change in size or color of a mole

Your healthcare provider should check your skin before you start taking ZELBORAF, and every 2 months during treatment with ZELBORAF, to look for any new skin cancers. Your healthcare provider may continue to check your skin for 6 months after you stop taking ZELBORAF.

Your healthcare provider should also check for cancers that may not occur on the skin. Tell your healthcare provider about any new symptoms that you get while taking ZELBORAF.

Other blood cell cancers have happened in some people with Erdheim-Chester Disease (ECD) including those who take ZELBORAF. If you have other blood cell cancers and take ZELBORAF for ECD, your healthcare provider will monitor your blood cancer through routine blood tests.

See "What are the possible side effects of ZELBORAF?" for more information about side effects.

What is ZELBORAF?

ZELBORAF is a prescription medicine used to treat:

- a type of skin cancer called melanoma that:
  - has spread to other parts of the body or cannot be removed by surgery, and
  - has a certain type of abnormal "BRAF" gene.

ZELBORAF is not used to treat melanoma with a normal BRAF gene.

Your healthcare provider will perform a test to make sure that ZELBORAF is right for you.

- a type of blood cell cancer called Erdheim-Chester Disease (ECD) that:
  - can affect body tissues and organs, and
  - has a certain type of abnormal "BRAF" gene.

It is not known if ZELBORAF is safe and effective in children under 18 years of age.

Before you take ZELBORAF, tell your healthcare provider about all of your medical conditions, including if you:

- have any heart problems, including a condition called long QT syndromes
- have liver or kidney problems
- have had or are planning to receive radiation therapy
- have been told that you have low blood levels of potassium, calcium, or magnesium
- are pregnant or plan to become pregnant. ZELBORAF can harm your unborn baby.
  - Females who are able to become pregnant should use effective birth control during treatment with ZELBORAF and for 2 weeks after the final dose of ZELBORAF.
  - Talk to your healthcare provider about birth control methods that may be right for you.
  - Tell your healthcare provider right away if you become pregnant or think you are pregnant during treatment with ZELBORAF.
- are breastfeeding or plan to breastfeed. It is not known if ZELBORAF passes into your breast milk. Do not breastfeed during treatment with ZELBORAF and for 2 weeks after the final dose of ZELBORAF. Talk to your healthcare provider about the best way to feed your baby during this time.

Tell your healthcare provider about all the medicines you take, including prescription and over-the-counter medicines, vitamins, and herbal supplements. Know the medicines you take. Keep a list of them to show your healthcare provider and pharmacist when you get a new medicine.

How should I take ZELBORAF?

- Take ZELBORAF exactly as your healthcare provider tells you. Do not change your dose or stop taking ZELBORAF unless your healthcare provider tells you to.
- Take ZELBORAF every 12 hours with or without a meal.
- Do not crush or chew ZELBORAF tablets.
- Do not take an additional dose of ZELBORAF if you vomit after taking your scheduled dose. Take your next dose at your regular time.
- If you miss a dose of ZELBORAF, take it as soon as you remember. If it is within 4 hours of your next scheduled dose, just take your next dose at your regular time. Do not make up for the missed dose.
- If you take too much ZELBORAF, call your healthcare provider or go the nearest hospital emergency room right away.

What should I avoid while taking ZELBORAF?

Avoid sunlight during treatment with ZELBORAF. ZELBORAF can make your skin sensitive to sunlight. You may burn more easily and get severe sunburns. To help protect against sunburn:

- When you go outside, wear clothes that protect your skin, including your head, face, hands, arms, and legs.
- Use lip balm and a broad-spectrum sunscreen with SPF 30 or higher.

What are the possible side effects of ZELBORAF?

ZELBORAF may cause serious side effects, including:

- See "What is the most important information I should know about ZELBORAF?"
- Allergic reactions can happen while taking ZELBORAF and can be severe. Stop taking ZELBORAF and get medical help right away if you get any of these symptoms of an allergic reaction:

- rash or redness all over your body
- trouble breathing or swallowing
- swelling of the face, lips, or tongue

- throat tightness or hoarseness
- feel faint
- a fast heartbeat

- Severe skin reactions. Stop taking ZELBORAF and call your healthcare provider right away if you get a skin rash with any of the following symptoms because you may have a severe skin reaction:

- blisters on your skin
- blisters or sores in your mouth
- peeling of your skin

- fever
- redness or swelling of your face, hands, or soles of your feet

- Changes in the electrical activity of your heart called QT prolongation. QT prolongation can cause irregular heartbeats that can be life-threatening. Your healthcare provider should do tests before you start taking ZELBORAF and during your treatment with ZELBORAF to check the electrical activity of your heart and your body salts (electrolytes). Tell your healthcare provider right away if you feel faint, lightheaded, dizzy, or feel your heart beating irregularly or fast while taking ZELBORAF. These may be symptoms related to QT prolongation.
- Liver injury. Your healthcare provider should do blood tests to check your liver function before you start taking ZELBORAF and during treatment. Tell your healthcare provider right away if you get any of these symptoms of a liver problem during treatment:
  - yellowing of your skin or the white part of your eyes
  - dark or brown (tea color) urine
  - nausea or vomiting
  - loss of appetite
  - pain on the right side of your stomach
- Eye problems. Tell your healthcare provider right away if you get any of these symptoms during treatment with ZELBORAF:
  - eye pain, swelling, or redness
  - blurred vision or other vision changes
- Worsening side effects from radiation treatment that can sometimes be severe or lead to death. Tell your healthcare provider if you have had or are planning to receive radiation therapy.
- Kidney injury. Your healthcare provider should do blood tests to check your kidney function before you start taking ZELBORAF and during treatment.
- Connective tissue disorders. Tell your healthcare provider if you develop an unusual thickening of the palms of your hands along with tightening of the fingers inward or any unusual thickening of the soles of your feet which may be painful.

The most common side effects of ZELBORAF in melanoma include:

- joint pain
- rash (see "Severe skin reactions" above)
- hair loss
- tiredness

□ sunburn or sun sensitivity
□ nausea
□ itching
□ warts

The most common side effects of ZELBORAF in Erdheim-Chester Disease include:

- joint pain
- rash
- warts

□ tiredness
□ hair loss

- QT prolongation (see "Changes in the electrical activity of your heart called QT prolongation" above)

These are not all the possible side effects of ZELBORAF.

Call your doctor for medical advice about side effects. You may report side effects to FDA at 1-800-FDA-1088.

You may also report side effects to Genentech at 1-888-835-2555.

How should I store ZELBORAF?

- Store ZELBORAF at room temperature between 68°F to 77°F (20°C to 25°C).
- Store ZELBORAF in the original container with the lid tightly closed.
- Ask your healthcare provider or pharmacist how to safely throw away (dispose of) any unused or expired ZELBORAF.

Keep ZELBORAF and all medicine out of the reach of children.

General information about the safe and effective use of ZELBORAF.

Medicines are sometimes prescribed for purposes other than those listed in a Medication Guide. Do not use ZELBORAF for a condition for which it was not prescribed. Do not give ZELBORAF to other people, even if they have the same symptoms that you have. It may harm them. You can ask your healthcare provider or pharmacist for information about ZELBORAF that is written for health professionals.

What are the ingredients in ZELBORAF?

Active ingredient: vemurafenib

Inactive ingredients:

Tablet Core: hypromellose acetate succinate, croscarmellose sodium, colloidal silicon dioxide, magnesium stearate, and hydroxypropyl cellulose.

Coating: pinkish white: poly (vinyl alcohol), titanium dioxide, polyethylene glycol 3350, talc, and iron oxide red.

Distributed by: Genentech USA, Inc., A Member of the Roche Group,1 DNA Way, South San Francisco, CA 94080-4990
ZELBORAF is a registered trademark of Genentech, Inc.
Co-promoted by: Genentech USA, Inc. and Daiichi Sankyo, Inc.
©2017 Genentech, Inc. For more information, go to www.ZELBORAF.com or call 1-877-436-3683.

This Medication Guide has been approved by the U.S. Food and Drug Administration

Revised: 11/2017

Representative sample of labeling (see the HOW SUPPLIED section for complete listing):

PRINCIPAL DISPLAY PANEL - 240 mg Tablet Bottle Carton

NDC 50242-090-02

Zelboraf®
(vemurafenib)
tablets

240 mg

Do not crush or chew tablet.

Rx only

Attention Pharmacist: Dispense the
accompanying Medication Guide to
each patient.

112 tablets

Genentech | Daiichi Sankyo, Inc.

10210025